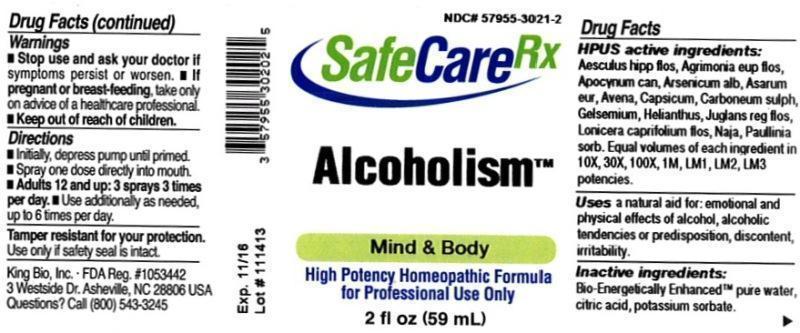 DRUG LABEL: Alcoholism
NDC: 57955-3021 | Form: LIQUID
Manufacturer: King Bio Inc.
Category: homeopathic | Type: HUMAN OTC DRUG LABEL
Date: 20131125

ACTIVE INGREDIENTS: AESCULUS HIPPOCASTANUM FLOWER 10 [hp_X]/59 mL; AGRIMONIA EUPATORIA FLOWER 10 [hp_X]/59 mL; APOCYNUM CANNABINUM ROOT 10 [hp_X]/59 mL; ARSENIC TRIOXIDE 10 [hp_X]/59 mL; ASARUM EUROPAEUM 10 [hp_X]/59 mL; AVENA SATIVA FLOWERING TOP 10 [hp_X]/59 mL; CAPSICUM 10 [hp_X]/59 mL; CARBON DISULFIDE 10 [hp_X]/59 mL; GELSEMIUM SEMPERVIRENS ROOT 10 [hp_X]/59 mL; HELIANTHUS ANNUUS FLOWERING TOP 10 [hp_X]/59 mL; JUGLANS REGIA FLOWERING TOP 10 [hp_X]/59 mL; LONICERA CAPRIFOLIUM FLOWERING TOP 10 [hp_X]/59 mL; NAJA NAJA VENOM 10 [hp_X]/59 mL; PAULLINIA CUPANA SEED 10 [hp_X]/59 mL
INACTIVE INGREDIENTS: WATER; CITRIC ACID MONOHYDRATE; POTASSIUM SORBATE

Alcoholism

Drug Facts

____________________________________________________________________________________________________________________

HPUS active ingredients: Aesculus hippocastanum, flos, Agrimonia eupatoria, flos, Apocynum cannabinum, Arsenicum album, Asarum europaeum, Avena sativa, Capsicum annuum, Carboneum sulphuratum, Gelsemium sempervirens, Helianthus annuus, Juglans regia, flos, Lonicera caprifolium, flos, Naja tripudians, Paullinia sorbilis. Equal volumes of each ingredient in 10X, 30X, 100X, 1M, LM1, LM2, LM3 potencies.

INDICATIONS AND USAGE

Uses a natural aid for: emotional and physical effects of alcohol, alcoholic tendencies or predisposition, discontent, irritability.

INACTIVE INGREDIENT

Inactive ingredients: Bio-Energetically Enhanced pure water, citric acid, potassium sorbate.

Warnings

- Stop use and ask your doctor if symptoms persist or worsen.
- If pregnant or breast-feeding, take only on advice of a healthcare professional.

- Keep out of reach of children.

Directions:

- Initially, depress pump until primed.
- Spray one dose directly into mouth.
- Adults 12 and up: 3 sprays 3 times per day.
- Use additionaly as needed, up to 6 times per day.

OTHER SAFETY INFORMATION

Tamper resistant for your protection. Use only if safety seal is intact.

PURPOSE

Uses a natural aid for:

- emotional and physical effects of alcohol
- alcoholic tendencies or predisposition
- discontent
- irritability.